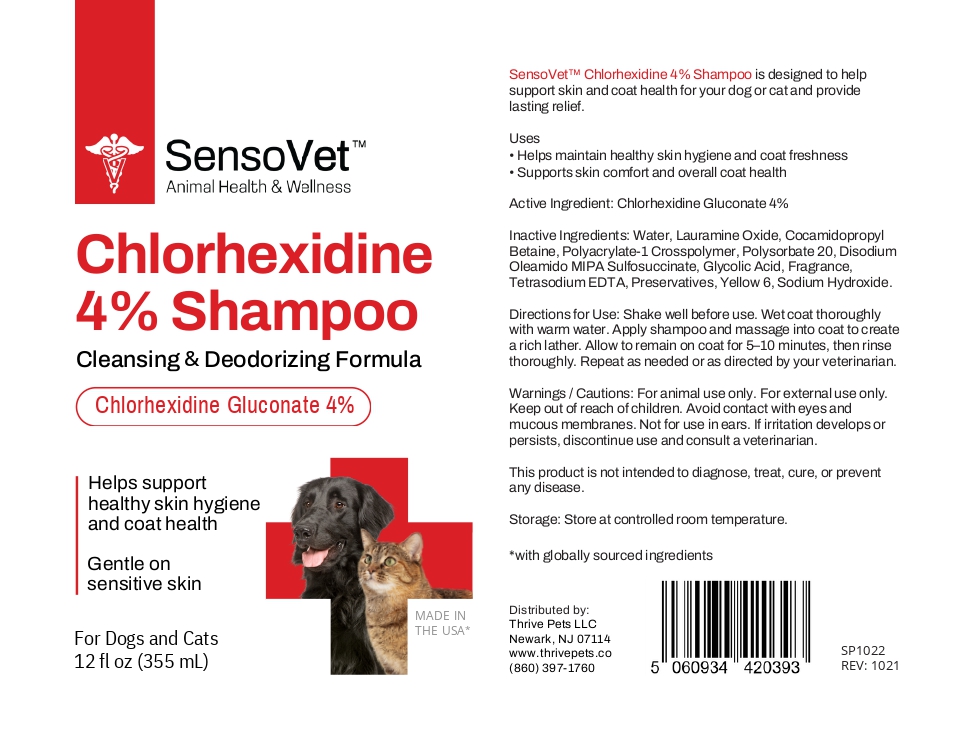 DRUG LABEL: Chlorhexidine Gluconate
NDC: 86219-200 | Form: Shampoo
Manufacturer: Thrive Pets LLC
Category: animal | Type: OTC ANIMAL DRUG LABEL
Date: 20250915

ACTIVE INGREDIENTS: CHLORHEXIDINE GLUCONATE 4 g/100 mL
INACTIVE INGREDIENTS: Water; Lauramine Oxide; Polyacrylate-1 Crosspolymer; Cocamidopropyl Betaine; DISODIUM OLEAMIDO MIPA-SULFOSUCCINATE; Glycolic Acid; FRAGRANCE 13576; TETRASODIUM EDTA; YELLOW 6; Sodium Hydroxide

SensoVet Chlorhexidine 4% Shampoo

DESCRIPTION

SensoVet Chlorhexidine 4% Shampoo is designed to help support skin and coat health for your dog or cat and provide lasting relief.

Active Ingredients:

Chlorhexidine Gluconate 4%

Inactive Ingredients:

Water, Lauramine Oxide, Cocamidopropyl Betaine, Polyacrylate-1 Crosspolymer, Polysorbate 20, Disodium Oleamido MIPA Sulfosuccinate, Glycolic Acid, Fragrance, Tetrasodium EDTA, Preservatives, Yellow 6, Sodium Hydroxide.

Indications

- Helps maintain healthy skin hygiene and coat freshness
- Supports skin comfort and overall coat health

Directions for Use:

- Shake well before use. Wet coat thoroughly with warm water.
- Apply shampoo and massage into coat to create a rich lather.
- Allow to remain on coat for 5–10 minutes, then rinse thoroughly.
- Repeat as needed or as directed by your veterinarian.

Warnings / Cautions:

- For animal use only. For external use only. Keep out of reach of children.
- Avoid contact with eyes and mucous membranes. Not for use in ears.
- If irritation develops or persists, discontinue use and consult a veterinarian.

STORAGE AND HANDLING

- Store at controlled room temperature.
- This product is not intended to diagnose, treat, cure, or prevent any disease.
- with globally sourced ingredients

Distributed by:

Thrive Pets LLC
Newark, NJ 07114
www.thrivepets.co

PRINCIPAL DISPLAY PANEL - 12 fl oz

SensoVet™

Chlorhexidine 4% Shampoo

Cleansing & Deodorizing Formula

Gentle on sensitive skin

Helps support healthy skin hygiene and coat health

For Dogs and Cats

12 fl oz (355 mL)